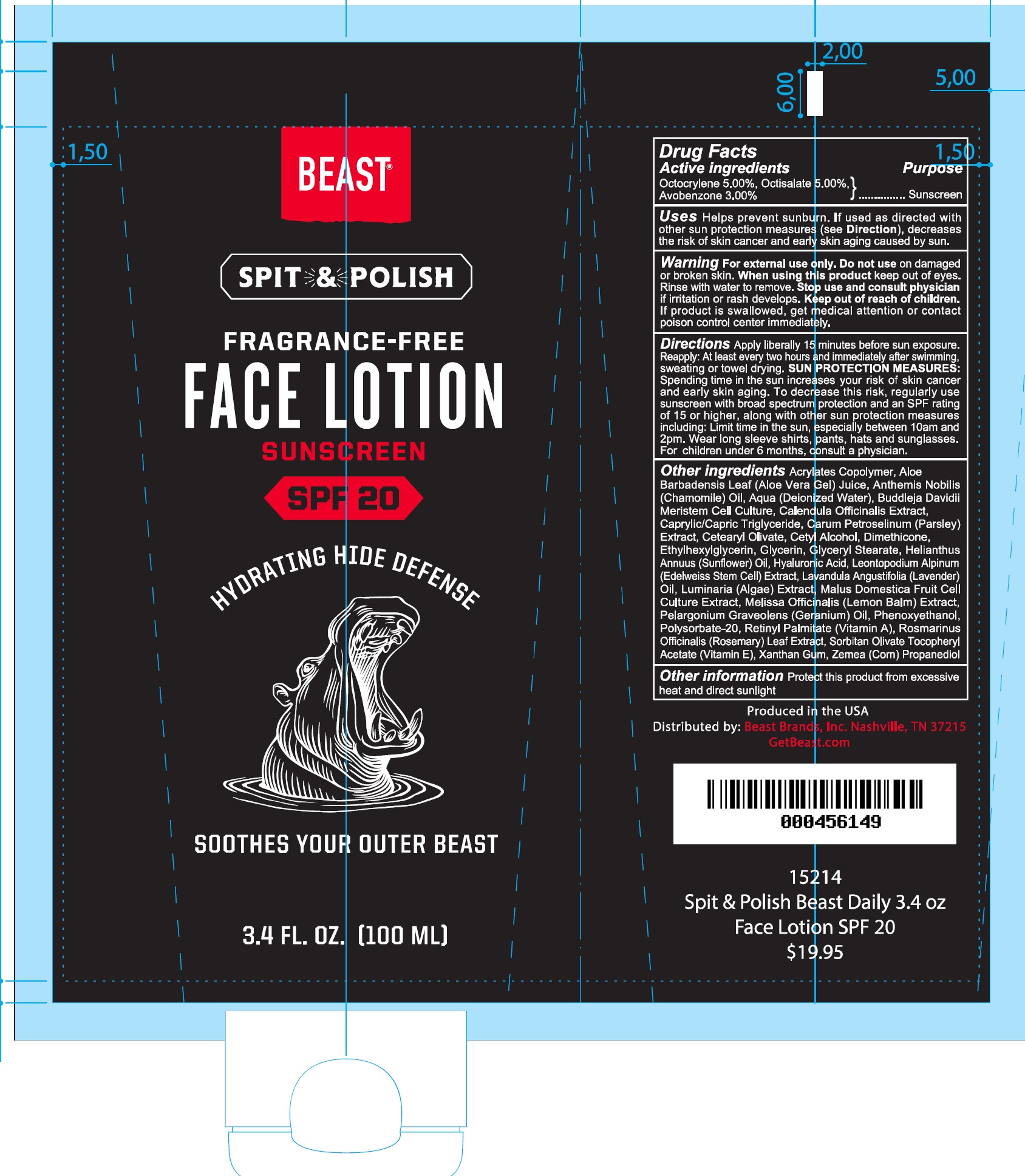 DRUG LABEL: BEAST SPIT and POLISH FACE SPF-20
NDC: 73095-385 | Form: LOTION
Manufacturer: Small Batch Beauty, LLC
Category: otc | Type: HUMAN OTC DRUG LABEL
Date: 20231111

ACTIVE INGREDIENTS: OCTOCRYLENE 50 mg/1 mL; OCTISALATE 50 mg/1 mL; AVOBENZONE 30 mg/1 mL
INACTIVE INGREDIENTS: ALOE VERA LEAF; CHAMAEMELUM NOBILE WHOLE; WATER; CALENDULA OFFICINALIS FLOWER; MEDIUM-CHAIN TRIGLYCERIDES; PETROSELINUM CRISPUM WHOLE; CETYL ALCOHOL; DIMETHICONE; ETHYLHEXYLGLYCERIN; GLYCERIN; GLYCERYL MONOSTEARATE; SUNFLOWER OIL; HYALURONIC ACID; LEONTOPODIUM NIVALE SUBSP. ALPINUM WHOLE FLOWERING; LAVENDER OIL; APPLE; MELISSA OFFICINALIS WHOLE; PELARGONIUM GRAVEOLENS FLOWER OIL; PHENOXYETHANOL; POLYSORBATE 20; VITAMIN A PALMITATE; ROSEMARY; SORBITAN OLIVATE; .ALPHA.-TOCOPHEROL ACETATE; XANTHAN GUM; CORN

BEAST SPIT and POLISH FACE LOTION SPF-20

Active ingredients

Octocrylene 5.00%, Octisalate 5.00%, Avobenzone 3.00%

Purpose

Sunscreen

Uses

Helps prevent sunburn. If used as directed with other sun protection measures (see), decreases the risk of skin cancer and early skin aging caused by the sun. Directions

Warnings

For externel use only

Do not use

on damaged or broken skin.

When using this product

- keep out of eyes. Rinse with water to remove.

Stop use and consult physician

if irritation or rash develops.

Keep out of reach of children.

If product is swallowed, get medical attention or contact poison control center immediately.

Directions

Apply liberally 15 minutes before sun exposure. Reapply:At least every two hours and immediately after swimming or sweating or towel drying. Spending time in the sun increases your risk of skin cancer and early skin aging. To decrease this risk, regularly use a sunscreen with broad spectrum protection and an SPF rating of 15 or higher, along with other sun protection measures including: Limit time in the sun, especially between 10am and 2pm. Wear long sleeve shirts, pants, hats, and sunglasses. For children under 6 months, consult a physician. SUN PROTECTION MEASURES:

Other ingredients

Acrylates Copolymer, Aloe Barbadensis Leaf (Aloe Vera Gel) Juice, Anthemis Nobilis (Chamomile) Oil,Aqua (Deionized Water), Buddleja Davidii Meristem Cell Culture, Calendula Officinalis Extract, Caprylic/Capric Triglyceride, Carum Petroselinum (Parsley) Extract,Cetearyl Olivate, Cetyl Alcohol, Dimethicone, Ethylhexylglycerin, Glycerin, Glyceryl Stearate, Helianthus Annuus (Sunflower)Oil, Hyaluronic Acid, Leontopodium Alpinum (Edelweiss Stem Cell) Extract, Lavandula Angustifolia (Lavender) Oil, Luminaria (Algae) Extract, Malus Domestica Fruit Cell Culture Extract, Melissa Officinalis (Lemon Balm) Extract, Pelargonium Graveolens (Geranium) Oil, Phenoxyethanol, Polysorbate-20, Retinyl Palmitate (Vitamin A), Rosmarinus Officinalis (Rosemary) Leaf Extract, Sorbitan Olivate, Tocopheryl Acetate (Vitamin E), Xanthan Gum, Zemea (Corn) Propanediol.

Other information

Protect the product from excessive heat and direct sunlight